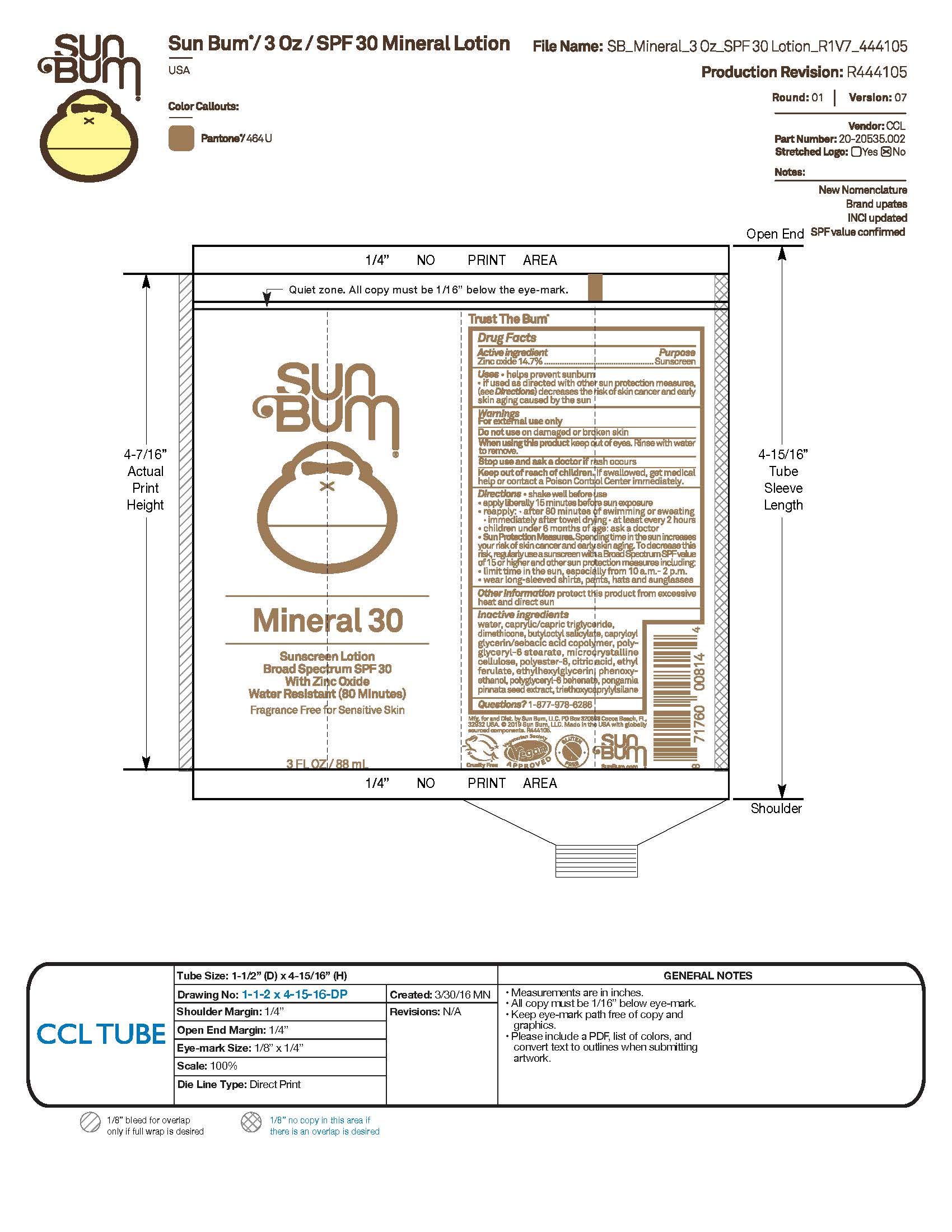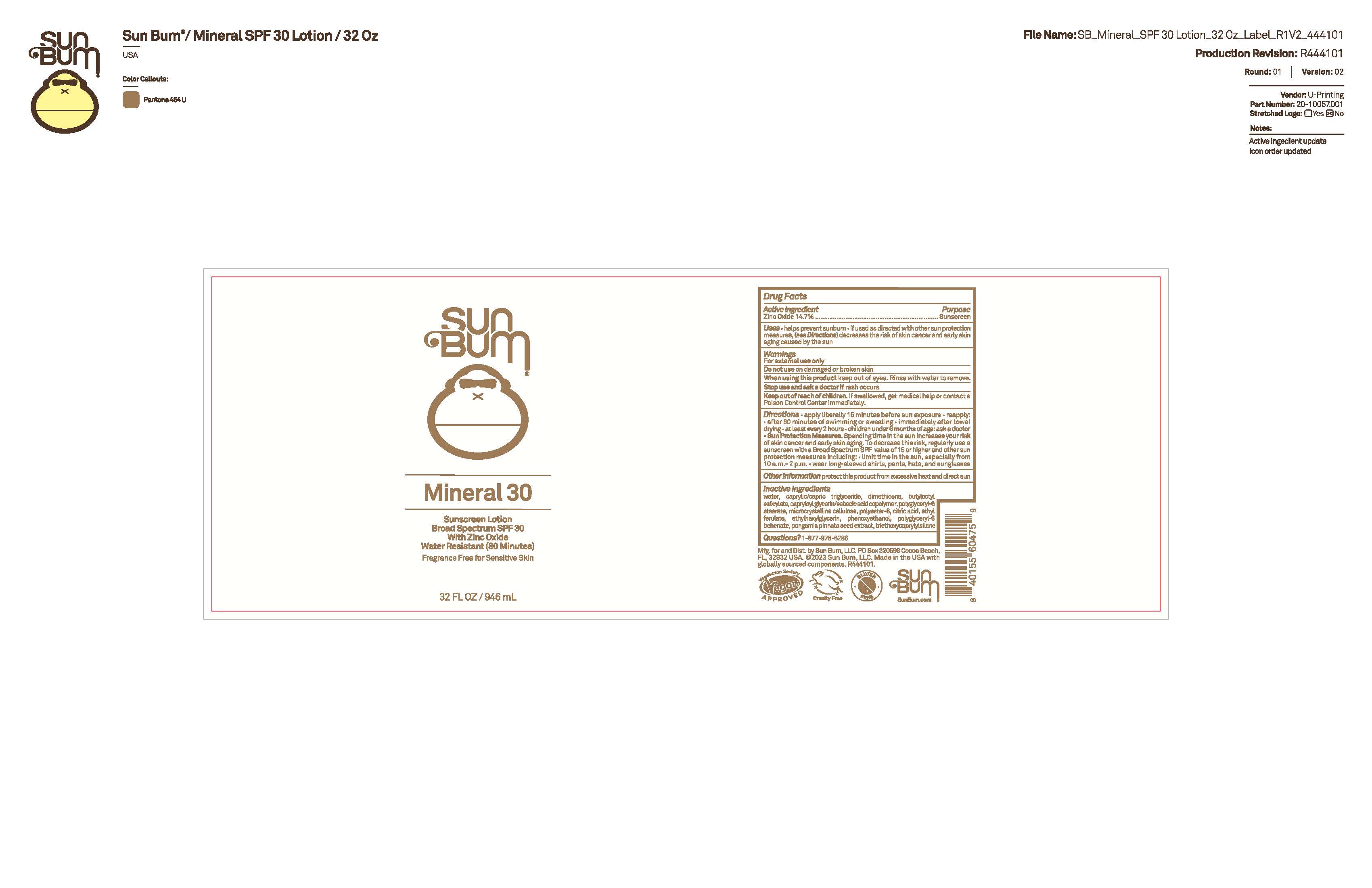 DRUG LABEL: Sun Bum Mineral 30 Sunscreen 3 OZ
NDC: 69039-749 | Form: LOTION
Manufacturer: Sun Bum, LLC
Category: otc | Type: HUMAN OTC DRUG LABEL
Date: 20250815

ACTIVE INGREDIENTS: ZINC OXIDE 147 mg/1 mL
INACTIVE INGREDIENTS: MICROCRYSTALLINE CELLULOSE; DIMETHICONE; CAPRYLOYL GLYCERIN/SEBACIC ACID COPOLYMER (2000 MPA.S); WATER; PHENOXYETHANOL; CAPRYLIC/CAPRIC TRIGLYCERIDE; BUTYLOCTYL SALICYLATE; POLYESTER-8 (1400 MW, CYANODIPHENYLPROPENOYL CAPPED); CITRIC ACID; PONGAMIA PINNATA SEED; POLYGLYCERYL-6 BEHENATE; TRIETHOXYCAPRYLYLSILANE; POLYGLYCERYL-6 STEARATE; ETHYL FERULATE; ETHYLHEXYLGLYCERIN

Sun Bum Mineral 30 Sunscreen 3 OZ, 32 OZ

Active Ingredients

Zinc Oxide 14.7%

Purpose

Sunscreen

Uses

• helps prevent sunburn • if used as directed with other sun protection measures, (see Directions) decreases the risk of skin cancer and early skin aging caused by the sun

Warnings

For external use only

Do not use on damaged or broken skin

When using this product keep out of eyes. Rinse with water to remove.

Stop use and ask a doctor if rash occurs

Keep out of reach of children. If swallowed, get medical help or contact a Poison Control Center immediately.

Warnings

Keep Out Of Reach Of Children

Directions

• shake well before use

• apply liberally 15 minutes before sun exposure

• reapply: • after 80 minutes of swimming or sweating • immediately after towel drying • at least every 2 hours

• children under 6 months of age: ask a doctor

• Sun Protection Measures. Spending time in the sun increases your risk of skin cancer and early skin aging. To decrease this risk, regularly use a sunscreen with a Broad Spectrum SPF value of 15 or higher and other sun protection measures including:

• limit time in the sun, especially from 10 a.m.- 2 p.m.

• wear long-sleeved shirts, pants, hats and sunglasses

Directions

• apply liberally 15 minutes before sun exposure

Other Information

protect this product from excessive heat and direct sun

Inactive Ingredients

water, caprylic/capric triglyceride, dimethicone, butyloctyl salicylate, capryloyl glycerin/sebacic acid copolymer, polyglyceryl-6 stearate, microcrystalline cellulose, polyester-8, citric acid, ethyl ferulate, ethylhexylglycerin, phenoxyethanol, polyglyceryl-6 behenate, pongamia pinnata seed extract, triethoxycaprylylsilane

Questions?

1-877-978-6286